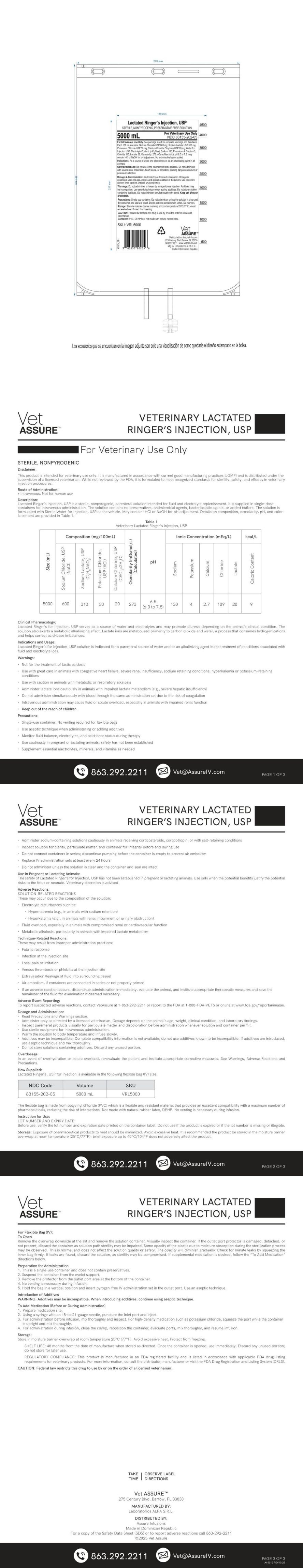 DRUG LABEL: Veterinary Lactated Ringers
NDC: 83155-202 | Form: INJECTION, SOLUTION
Manufacturer: Assure Infusion Inc
Category: animal | Type: PRESCRIPTION ANIMAL DRUG LABEL
Date: 20260223

ACTIVE INGREDIENTS: SODIUM LACTATE 310 mg/100 mL; SODIUM CHLORIDE 600 mg/100 mL; POTASSIUM CHLORIDE 30 mg/100 mL; CALCIUM CHLORIDE 20 mg/100 mL
INACTIVE INGREDIENTS: WATER

Veterinary Lactated Ringers

Dosage and Administration Section

As directed by a licensed veterinarian. Dosage is dependent upon the age, weight and clinical condition of the patient. Use the entire content once opened. Discard unused portion.